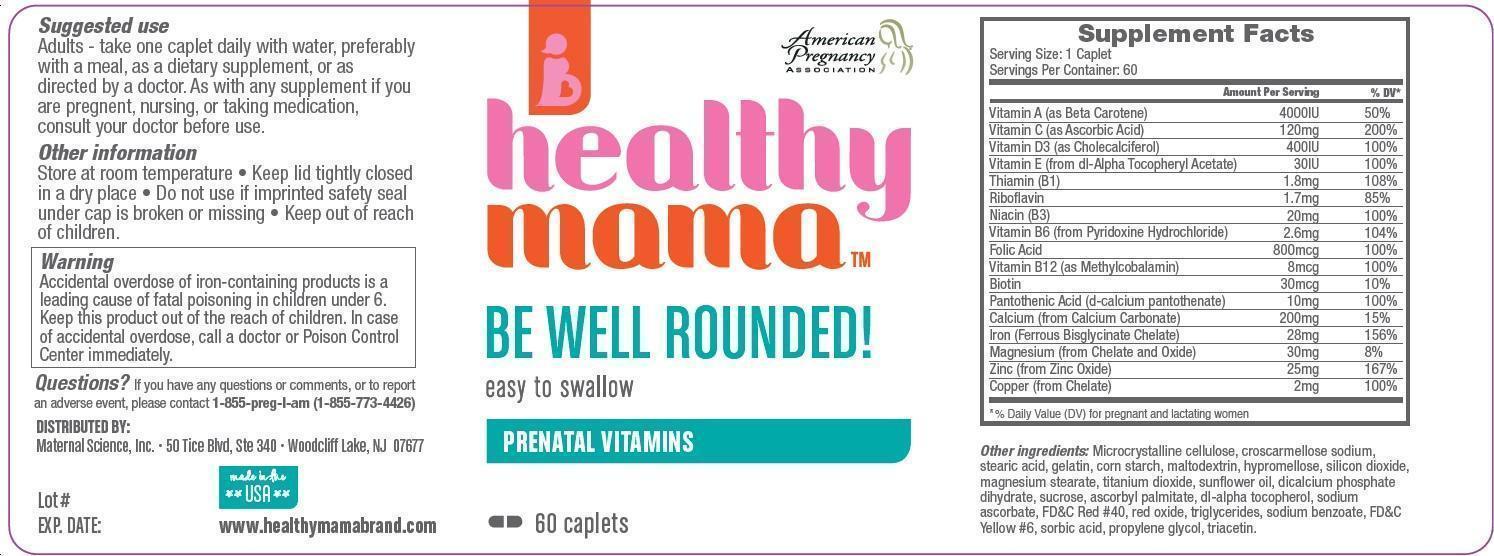 DRUG LABEL: healthy mamaBE WELL ROUNDED
 
NDC: 58154-107 | Form: TABLET, FILM COATED
Manufacturer: MATERNAL SCIENCE, LLC
Category: prescription | Type: HUMAN PRESCRIPTION DRUG LABEL
Date: 20130709

ACTIVE INGREDIENTS: .BETA.-CAROTENE 4000 [iU]/1 1; ASCORBIC ACID 120 mg/1 1; CHOLECALCIFEROL 400 [iU]/1 1; .ALPHA.-TOCOPHEROL ACETATE, DL- 30 [iU]/1 1; THIAMINE 1.8 mg/1 1; RIBOFLAVIN 1.7 mg/1 1; NIACIN 20 mg/1 1; PYRIDOXINE HYDROCHLORIDE 2.6 mg/1 1; FOLIC ACID 800 ug/1 1; METHYLCOBALAMIN 8 ug/1 1; CALCIUM CARBONATE 200 mg/1 1; FERROUS BISGLYCINATE 28 mg/1 1; ZINC OXIDE 25 mg/1 1; COPPER 2 mg/1 1; BIOTIN 30 ug/1 1; CALCIUM PANTOTHENATE 10 mg/1 1; MAGNESIUM OXIDE 30 mg/1 1
INACTIVE INGREDIENTS: ASCORBYL PALMITATE; CROSCARMELLOSE SODIUM; CALCIUM PHOSPHATE, DIBASIC, ANHYDROUS; FD&C RED NO. 40; FD&C YELLOW NO. 6; GELATIN; HYPROMELLOSES; MAGNESIUM STEARATE; MALTODEXTRIN; CELLULOSE, MICROCRYSTALLINE; .ALPHA.-TOCOPHEROL; STARCH, CORN; PROPYLENE GLYCOL; SILICON DIOXIDE; SODIUM ASCORBATE; SODIUM BENZOATE; SORBIC ACID; STEARIC ACID; SUCROSE; SUNFLOWER OIL; TITANIUM DIOXIDE; TRIACETIN

healthy mama PRENATAL VITAMINS

Supplement Facts

Serving Size: 1 caplet

Serving per Container: 60

Annual Per Serving % DV*

Vitamin A (as beta Carotene) 4000IU 50%

Vitamin C (as Ascorbic Acid) 120mg 200%

Vitamin D3 (as Cholecalciferol) 400IU 100%

Vitamin E(from dl-Alpha Tocopheryl Acetate) 30IU 100%

Thiamin (B1) 1.8mg 108%

Riboflavin 1.7mg 85%

Niacin (B3) 20mg 100%

Vitamin B6 (from Pyridoxine Hydrocholride) 2.6mg 104%

Folic Acid 800mcg 100%

Vitamin B12(as Methylcobalamin) 8mcg 100%

Biotin 30 mcg 10%

Pantothenic Acid(d-Calcium Patothenate) 10 mg 100%

Calcium(from Calcium Carbonate) 200 mg 15%

iron(Ferrous Bisglycinate Chelate) 28 mg 156%

Magnesium (from Chelate and oxide) 30 mg 8%

Zinc (from Zinc Oxide) 25 mg 167%

Copper (from Chelate) 2 mg 100%

% Daily value9DV) for pregnant and lactating women

Other ingredients: Microcrystalline cellulose, croscarmellose sodium, stearic acid, gelatin, corn starch, maltodextrin, hypromellose, silicon dioxide, magnesium stearate, titanium dioxide , sunflower oil, dicalcium phosphate dihydrate, sucrose, Ascorbyl palmitate, dl-alpha tocopherol, sodium ascorbate, FD and C Red #40, red oxide, triglycerides, sodium benzoate, FD and C Yellow # 6, sorbic acid, propylene glycol, triacetin

INDICATIONS AND USAGE

PRENATAL VITAMINS

Suggested Use

Adults-take one caplet daily with water, preferably with a mean, as a dietary supplement, or as directed by doctor. As with any supplement if you are pregnent, nursing, or taking medication.consult your doctor before use.

Warning

Warning: Accidental overdose of iron containing products is a leading cause of fatal poisoning in children under age 6. Keep this product out of the reach of children. In case of accidental overdose, call a doctor or poison control center immediately.

Precautions

Folic Acid may partially correct the hematological damage due to vitamin B12 deficiency of pernicious anemia, while the associated neurological damage progresses.

Other information

Store at a room temperature.

- Keep lid tightly closed in a dry place
- Do not use if imprinted safety seal under cap is broken or missing
- keep out of reach of children

Questions?

If you have any questions or comments, or to report an adverse event, please contact 1-855-preg-i-am(1-855-773-4426)

Principal Display Panel

American Pregnancy Association

healthy mama

BE WELL ROUNDED!

easy to swallow

PRENATAL VITAMINS

60 caplets

DISTRIBUTED BY:

Maternal Science, Inc

50 Tice Blvd, Ste 340, woodcliff Lake ,Nj 07677

www.healthymamabrand.com